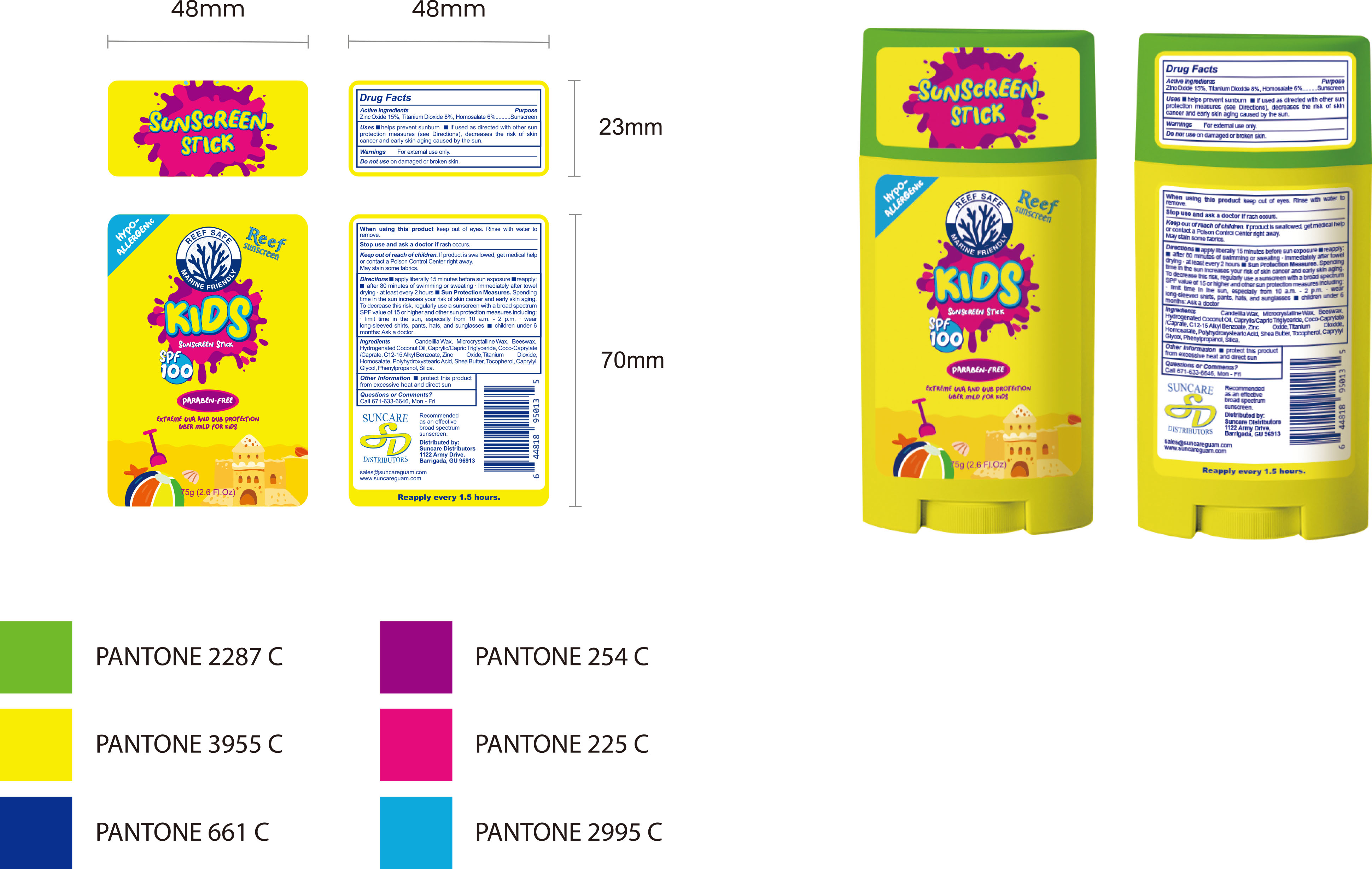 DRUG LABEL: SUNSCREEN Stick
NDC: 84938-005 | Form: STICK
Manufacturer: Foshan Sugar Max Cosmetics CO.,Ltd
Category: otc | Type: HUMAN OTC DRUG LABEL
Date: 20251216

ACTIVE INGREDIENTS: TITANIUM DIOXIDE 0.08 g/1 g; HOMOSALATE 0.06 g/1 g; ZINC OXIDE 0.15 g/1 g
INACTIVE INGREDIENTS: TOCOPHEROL; OCTISALATE; POLYHYDROXYSTEARIC ACID (2300 MW); CANDELILLA WAX; MICROCRYSTALLINE WAX; BEESWAX; HYDROGENATED COCONUT OIL; COCOYL CAPRYLOCAPRATE; SHEA BUTTER; PHENYLPROPANOL; SILICA; CAPRYLYL GLYCOL; CAPRYLIC/CAPRIC TRIGLYCERIDE; ALKYL (C12-15) BENZOATE

84938-005 SUNSCREEN STICK

ACTIVE INGREDIENT

Zinc Oxide 15%, Titanium Dioxide 8%, Homosalate 6%

PURPOSE

Sunscreen

INDICATIONS AND USAGE

Uses helps prevent sunburn if used as directed with other sun protection measures (see Directions), decreases the risk of skin cancer and early skin aging caused by the sun.

WARNINGS

For external use only.

Do not use on damaged or broken skin.

When using this product keep out of eyes. Rinse with water to remove.

Stop use and ask a doctor if rash occurs.

KEEP OUT OF REACH OF CHILDREN

Keep out ofreach ofchildren. lf product is swallowed, get medical help or contact a Poison Control Center right away.May stain some fabrics.

DOSAGE AND ADMINISTRATION

Directions apply liberally 15 minutes before sun exposure reapply:after 80 minutes of swimming or sweating . lmmediately after towel drying ·at least every 2 hours Sun Protection Measures. Spending time in the sun increases your risk of skin cancer and early skin aging To decrease this risk, regularly use a sunscreen with a broad spectrum SPF value of 15 or higher and other sun protection measures including. limit time in the sun,especially from 10 a.m.-2 p.m.· wear long-sleeved shirts, pants, hats, and sunglasses children under 6 months: Ask a doctor

INACTIVE INGREDIENT

Candelilla Wax
Microcrystalline Wax
Beeswax
Hydrogenated Coconut Oil
Caprylic/Capric Triglyceride
Coco‑Caprylate/Caprate
C12‑15 Alkyl Benzoate
Octisalate (Ethylhexyl Salicylate)
Polyhydroxystearic Acid
Shea Butter (Butyrospermum Parkii Butter)
Tocopherol
Caprylyl Glycol
Phenylpropanol
Silica